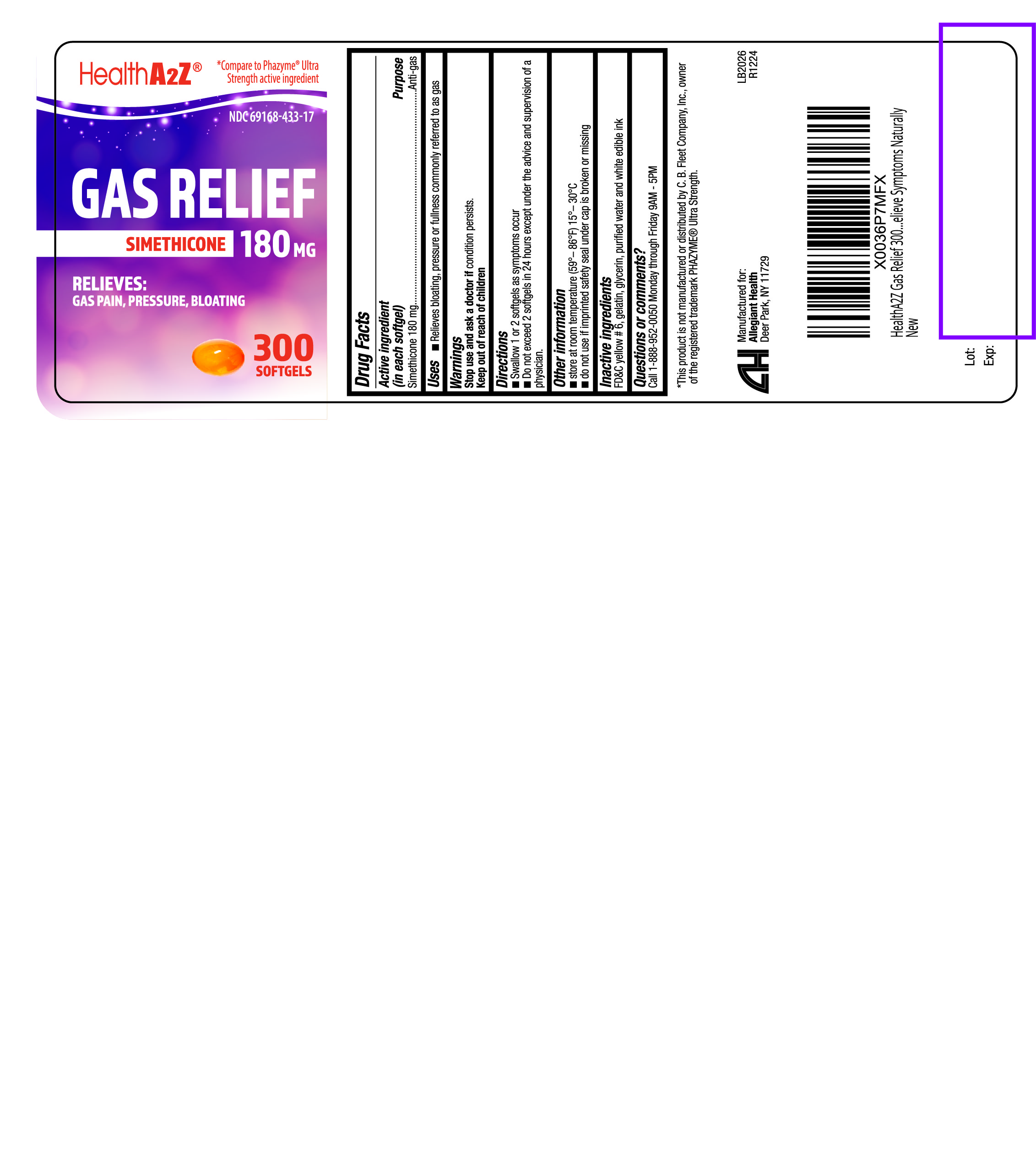 DRUG LABEL: Gas Relief
NDC: 69168-433 | Form: CAPSULE, LIQUID FILLED
Manufacturer: Allegiant Health
Category: otc | Type: HUMAN OTC DRUG LABEL
Date: 20210924

ACTIVE INGREDIENTS: DIMETHICONE 180 mg/1 1
INACTIVE INGREDIENTS: FD&C YELLOW NO. 6; GELATIN; GLYCERIN; WATER

433 - Gas Relief

Active ingredient(s)

Simethicone 180 mg

Purpose

Anti-gas

Use(s)

Relieves bloating, pressure or fullness commonly referred to as gas

Warnings

Stop use and ask a doctor if

condition persists.

Directions

- Swallow 1 or 2 softgels as symptoms
  occur
- Do not exceed 2 softgels in 24 hours
  except under the advice and
  supervision of a physician.

Other information

Do not use if imprinted safety seal under cap is broken or missing

Storage

- store at room temperature (59°– 86°F) 15°– 30°C

Inactive ingredients

FD&C yellow # 6, gelatin, glycerin,
purified water and white edible ink

Questions

Call 1-888-952-0050 Monday through Friday 9AM - 5PM

Principal Display Panel

Gas Relief